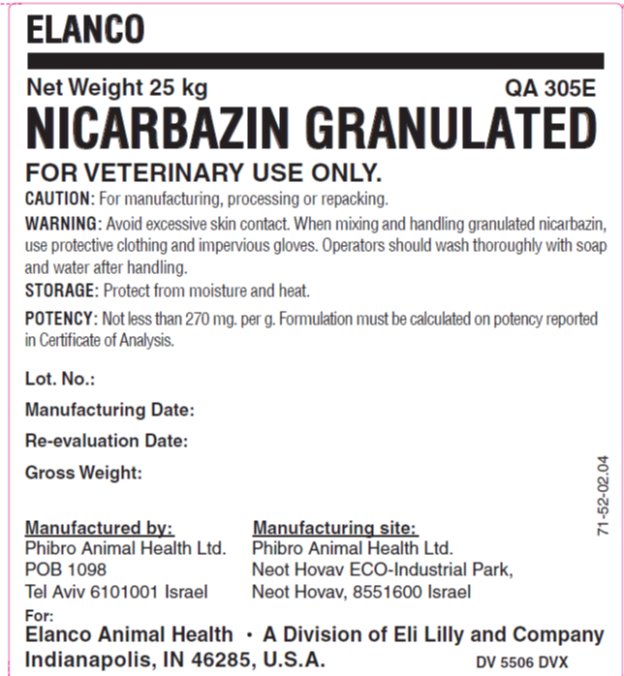 DRUG LABEL: Nicarbazin
NDC: 54277-2602 | Form: POWDER
Manufacturer: Phibro Animal Health LTD
Category: other | Type: BULK INGREDIENT - ANIMAL DRUG
Date: 20231120

ACTIVE INGREDIENTS: NICARBAZIN 100 kg/100 kg

NICARBAZIN

Label

Nicarbazin Label